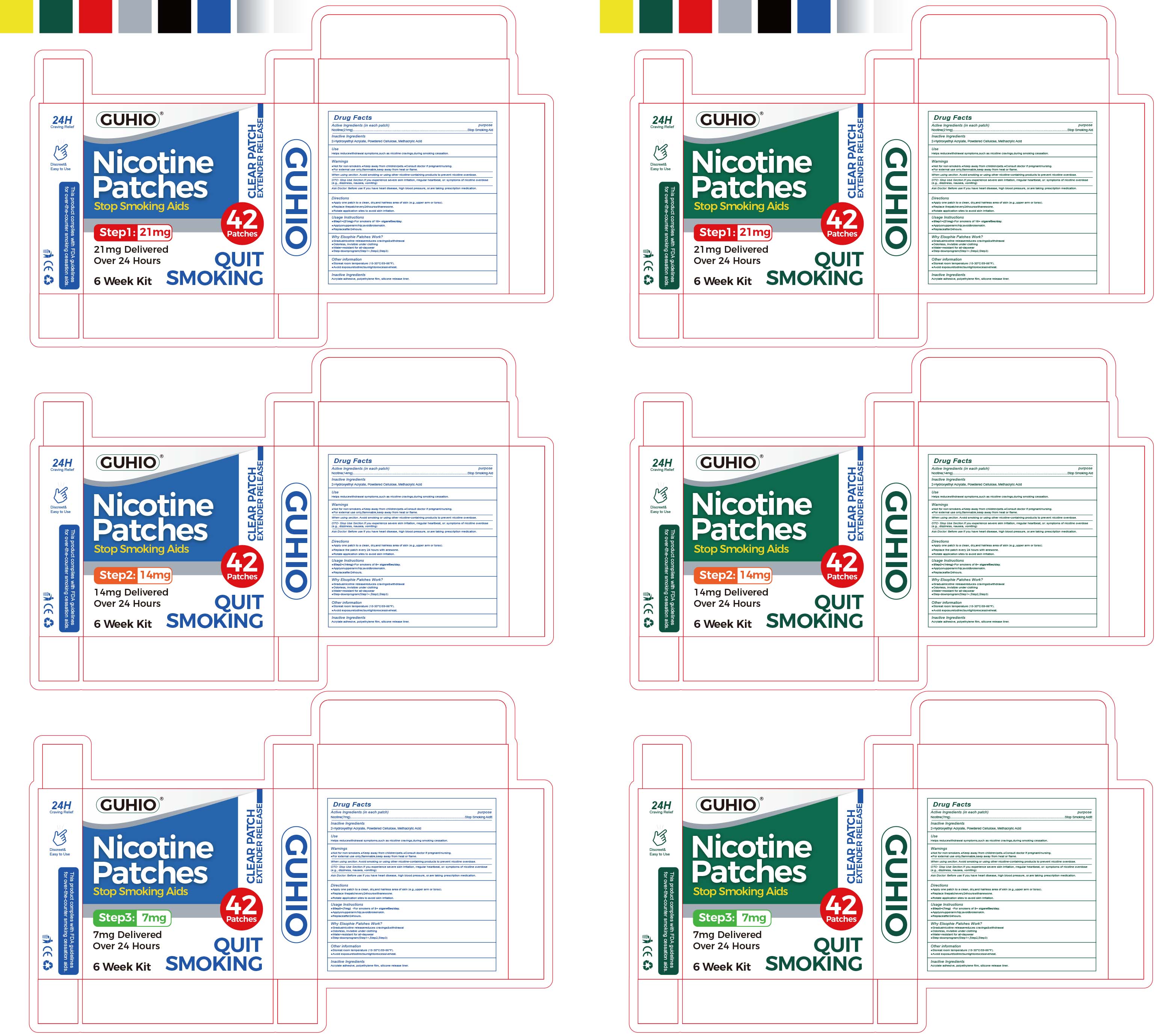 DRUG LABEL: GUHIO Nicotine Patch
NDC: 87278-001 | Form: PATCH
Manufacturer: Guangxi Keyun E-commerce Co., Ltd.
Category: otc | Type: HUMAN OTC DRUG LABEL
Date: 20251210

ACTIVE INGREDIENTS: NICOTINE 21 mg/1 1
INACTIVE INGREDIENTS: POWDERED CELLULOSE; 2-HYDROXYETHYL ACRYLATE; METHACRYLIC ACID

87278-001 GUHIO Nicotine Patch

ACTIVE INGREDIENT

Nicotine

PURPOSE

Stop Smoking Aid

INDICATIONS AND USAGE

Helps reducewithdrawal symptoms,such as nicotine cravings,during smoking cessation.

WARNINGS

Not for non-smokers. Keep away from children/pets. Consult doctor if pregnant/nursing
For external use only.flammable,keep away from heat or flame.

Not for non-smokers.

WHEN USING

When using section. Avoid smoking or using other nicotine-containing products to prevent nicotine overdose
Ask Doctor. Before use if you have heart disease, high blood pressure, or.are taking prescription medication.

STOP USE

OTC- Stop Use Section.lf you experience severe skin iritation, rregular heartbeat, or: symptoms of nicotine overdose (e.g.,dizziness, nausea, vomiting)

KEEP OUT OF REACH OF CHILDREN

Keep away from children/pets. Consult doctor if pregnant/nursing

DOSAGE AND ADMINISTRATION

Apply one patch to a clean, dry,and hairless area of skin (e.g.,upper arm or torso)
Replace thepatchevery24hourswithanewone
Rotate application sites to avoid skin irritation

INACTIVE INGREDIENT

2-Hydroxyethyl Acrylate, Powdered Cellulose, Methacrylic Acid